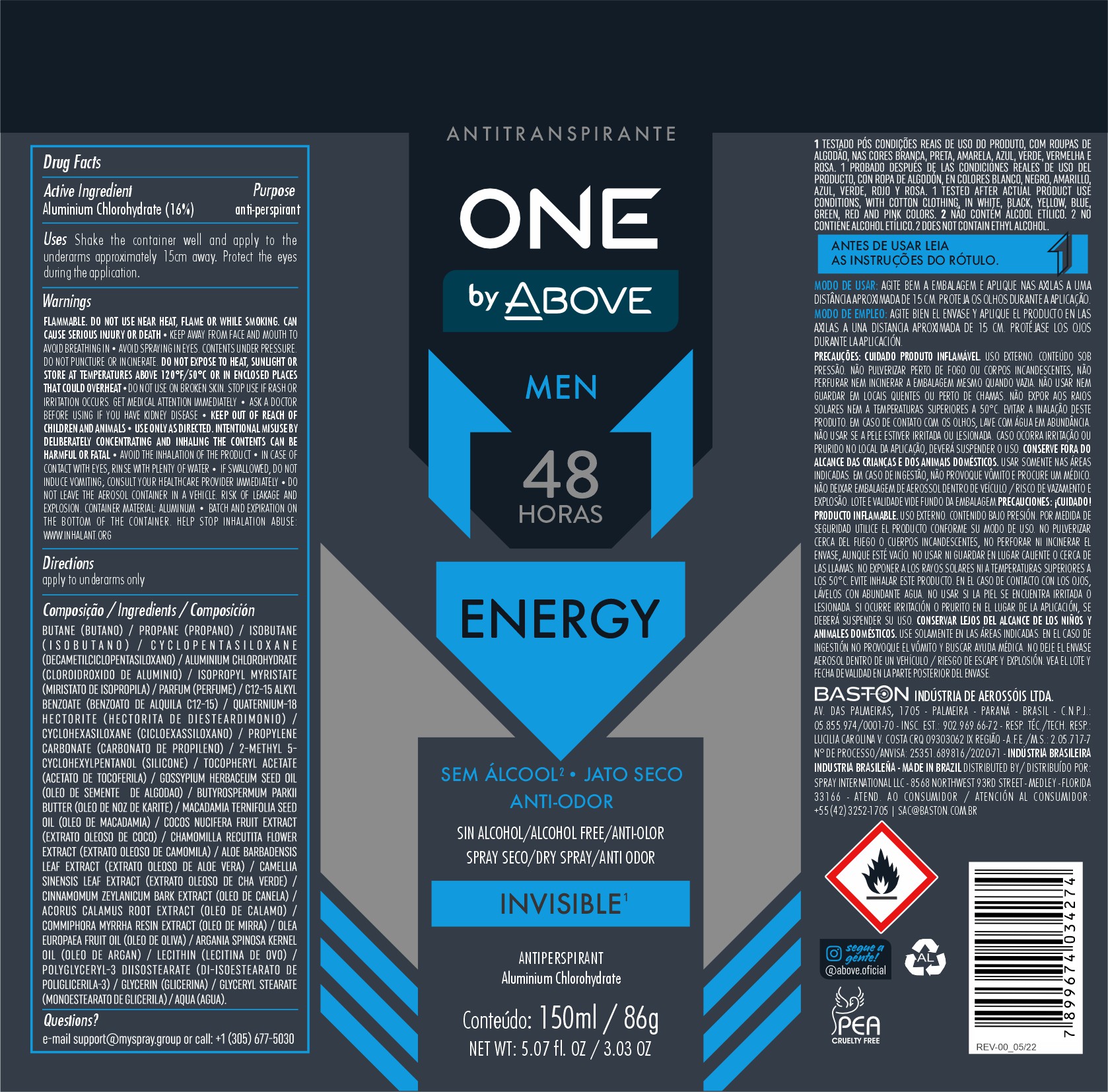 DRUG LABEL: ANTIPERSPIRANT ABOVE ONE BY ENERGY MEN
NDC: 73306-1150 | Form: AEROSOL, SPRAY
Manufacturer: BASTON INDUSTRIA DE AEROSSOIS LTDA
Category: otc | Type: HUMAN OTC DRUG LABEL
Date: 20241226

ACTIVE INGREDIENTS: ALUMINUM CHLOROHYDRATE 16 g/100 g
INACTIVE INGREDIENTS: ISOBUTANE

ANTIPERSPIRANT ABOVE ONE BY ENERGY MEN

Aluminium Chlorohydrate

UNDERARM ANTIPERSPIRANT DEODORANT

Shake the container well and apply to the underarms approximately 15cm away. Protect the eyes during the application.

INACTIVE INGREDIENT

BUTANE/ PROPANE/ ISOBUTANE/ CYCLOPENTASILOXANE/ ALUMINUM SESQUICHLOROHYDRATE/ ISOPROPYL MYRISTATE/
C12-15 ALKYL BENZOATE/ QUATERNIUM-18 HECTORITE/ CYCLOHEXASILOXANE/ PROPYLENE CARBONATE/ 2-METHYL 5-CYCLOHEXYLPENTANOL/
TOCOPHERYL ACETATE/ GOSSYPIUM HERBACEUM SEED OIL/ BUTYROSPERMUM PARKII BUTTER/ MACADAMIA TERNIFOLIA SEED OIL/ COCOS NUCIFERA FRUIT EXTRACT/ CHAMOMILLA RECUTITA FLOWER EXTRACT/
ALOE BARBADENSIS LEAF EXTRACT/ CAMELLIA SINENSIS LEAF EXTRACT/ CINNAMOMUM ZEYLANICUM BARK EXTRACT/ ACORUS CALAMUS ROOT EXTRACT/ COMMIPHORA MYRRHA RESIN EXTRACT/
OLEA EUROPAEA FRUIT OIL/ ARGANIA SPINOSA KERNEL OIL/ LECITHIN/ POLYGLYCERYL-3 DIISOSTEARATE/ GLYCERIN/ GLYCERYL STEARATE/ AQUA/
PARFUM, BENZYL SALICYLATE, COUMARIN, BENZYL BENZOATE, HYDROXYCITRONELLAL, GERANIOL

WARNINGS AND PRECAUTIONS

FLAMMABLE. DO NOT USE NEAR HEAT, FLAME OR WHILE SMOKING. CAN CAUSE SERIOUS INJURY OR DEATH KEEP AWAY FROM FACE AND MOUTH TO AVOID BREATHING IN AVOID SPRAYING IN EYES. CONTENTS UNDER PRESSURE. DO NOT PUNCTURE OR INCINERATE. DO NOT EXPOSE TO HEAT, SUNLIGHT OR STORE AT TEMPERATURES ABOVE 120°F/50°C OR IN ENCLOSED PLACES THAT COULD OVERHEAT DO NOT USE ON BROKEN SKIN. STOP USE IF RASH OR IRRITATION OCCURS. GET MEDICAL ATTENTION IMMEDIATELY ASK A DOCTOR BEFORE USING IF YOU HAVE KIDNEY DISEASE KEEP OUT OF REACH OF CHILDREN AND ANIMALS USE ONLY AS DIRECTED. INTENTIONAL MISUSE BY DELIBERATELY CONCENTRATING AND INHALING THE CONTENTS CAN BE HARMFUL OR FATAL AVOID THE INHALATION OF THE PRODUCT IN CASE OF CONTACT WITH EYES, RINSE WITH PLENTY OF WATER IF SWALLOWED, DO NOT INDUCE VOMITING; CONSULT YOUR HEALTHCARE PROVIDER IMMEDIATELY DO NOT LEAVE THE AEROSOL CONTAINER IN A VEHICLE. RISK OF LEAKAGE AND EXPLOSION. CONTAINER MATERIAL: ALUMINUM BATCH AND EXPIRATION ON THE BOTTOM OF THE CONTAINER. HELP STOP INHALATION ABUSE: WWW.INHALANT.ORG

WARNINGS

FLAMMABLE. DO NOT USE NEAR HEAT, FLAME OR WHILE SMOKING. CAN CAUSE SERIOUS INJURY OR DEATH KEEP AWAY FROM FACE AND MOUTH TO AVOID BREATHING IN AVOID SPRAYING IN EYES. CONTENTS UNDER PRESSURE. DO NOT PUNCTURE OR INCINERATE. DO NOT EXPOSE TO HEAT, SUNLIGHT OR STORE AT TEMPERATURES ABOVE 120°F/50°C OR IN ENCLOSED PLACES THAT COULD OVERHEAT DO NOT USE ON BROKEN SKIN. STOP USE IF RASH OR IRRITATION OCCURS. GET MEDICAL ATTENTION IMMEDIATELY ASK A DOCTOR BEFORE USING IF YOU HAVE KIDNEY DISEASE KEEP OUT OF REACH OF CHILDREN AND ANIMALS USE ONLY AS DIRECTED. INTENTIONAL MISUSE BY DELIBERATELY CONCENTRATING AND INHALING THE CONTENTS CAN BE HARMFUL OR FATAL AVOID THE INHALATION OF THE PRODUCT IN CASE OF CONTACT WITH EYES, RINSE WITH PLENTY OF WATER IF SWALLOWED, DO NOT INDUCE VOMITING; CONSULT YOUR HEALTHCARE PROVIDER IMMEDIATELY DO NOT LEAVE THE AEROSOL CONTAINER IN A VEHICLE. RISK OF LEAKAGE AND EXPLOSION. CONTAINER MATERIAL: ALUMINUM BATCH AND EXPIRATION ON THE BOTTOM OF THE CONTAINER. HELP STOP INHALATION ABUSE: WWW.INHALANT.ORG

DOSAGE AND ADMINISTRATION

make use of it whenever you find it necessary

KEEP OUT OF REACH OF CHILDREN

QUESTIONS

MAIL : SUPPORT@MYSPRAY.GROUP OR CALL (305) 677-5030